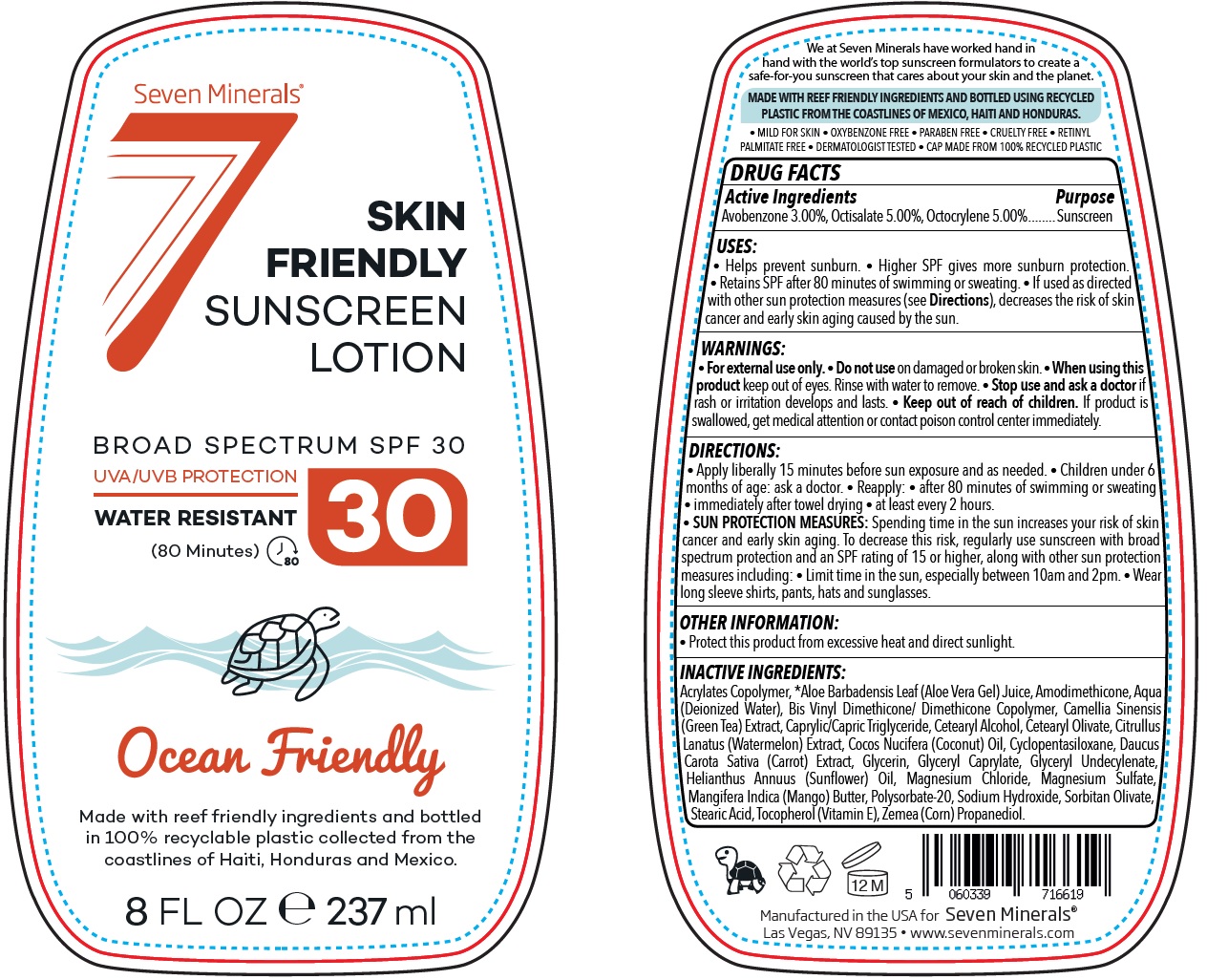 DRUG LABEL: SEVEN MINERALS Skin Friendly SPF 30
NDC: 73609-220 | Form: LOTION
Manufacturer: Seven Minerals NA LLC
Category: otc | Type: HUMAN OTC DRUG LABEL
Date: 20231111

ACTIVE INGREDIENTS: AVOBENZONE 30 mg/1 mL; OCTISALATE 50 mg/1 mL; OCTOCRYLENE 50 mg/1 mL
INACTIVE INGREDIENTS: BUTYL ACRYLATE/METHYL METHACRYLATE/METHACRYLIC ACID COPOLYMER (18000 MW); ALOE VERA LEAF; WATER; GREEN TEA LEAF; MEDIUM-CHAIN TRIGLYCERIDES; CETOSTEARYL ALCOHOL; CETEARYL OLIVATE; WATERMELON; COCONUT OIL; CYCLOMETHICONE 5; CARROT; GLYCERIN; GLYCERYL CAPRYLATE; GLYCERYL 1-UNDECYLENATE; HELIANTHUS ANNUUS FLOWERING TOP; MAGNESIUM CHLORIDE; MAGNESIUM SULFATE, UNSPECIFIED FORM; MANGO; POLYSORBATE 20; SODIUM HYDROXIDE; SORBITAN OLIVATE; STEARIC ACID; TOCOPHEROL; CORN; PROPANEDIOL

SEVEN MINERALS Skin Friendly SPF-30

Active Ingredients

Avobenzone 3.00%, Octisalate 5.00%, Octocrylene 5.00%

Purpose

Sunscreen

USES:

• Helps prevent sunburn. • Higher SPF gives more sunburn protection. • Retains SPF after 80 minutes of swimming or sweating. • If used as directed with other sun protection measures (see), decreases the risk of skin cancer and early skin aging caused by the sun. Directions

WARNINGS:

• For external use only

Do not use

- on damaged or broken skin.

When using this product

- keep out of eyes. Rinse with water to remove.

Stop use and ask a doctor

- if rash or irritation develops and lasts.

Keep out of reach of children.

- If product is swallowed, get medical attention or contact poison control center immediately.

DIRECTIONS:

• Apply liberally 15 minutes before sun exposure and as needed. • Children under 6 months of age: ask a doctor. • Reapply: • after 80 minutes of swimming or sweating • immediately after towel drying • at least every 2 hours. • Spending time in the sun increases your risk of skin cancer and early skin aging. To decrease this risk, regularly use sunscreen with broad spectrum protection and an SPF rating of 15 or higher, along with other sun protection measures including: • Limit time in the sun, especially between 10am and 2pm. • Wear long sleeve shirts, pants, hats and sunglasses.
SUN PROTECTION MEASURES:

OTHER INFORMATION:

• Protect this product from excessive heat and direct sunlight.

INACTIVE INGREDIENTS:

Acrylates Copolymer, *Aloe Barbadensis Leaf (Aloe Vera Gel) Juice, Amodimethicone, Aqua (Deionized Water), Bis Vinyl Dimethicone/ Dimethicone Copolymer, Camellia Sinensis (Green Tea) Extract, Caprylic/Capric Triglyceride, Cetearyl Alcohol, Cetearyl Olivate, Citrullus Lanatus (Watermelon) Extract, Cocos Nucifera (Coconut) Oil, Cyclopentasiloxane, Daucus Carota Sativa (Carrot) Extract, Glycerin, Glyceryl Caprylate, Glyceryl Undecylenate, Helianthus Annuus (Sunflower) Oil, Magnesium Chloride, Magnesium Sulfate, Mangifera Indica (Mango) Butter, Polysorbate-20, Sodium Hydroxide, Sorbitan Olivate, Stearic Acid, Tocopherol (Vitamin E), Zemea (Corn) Propanediol.